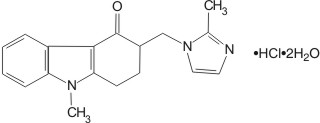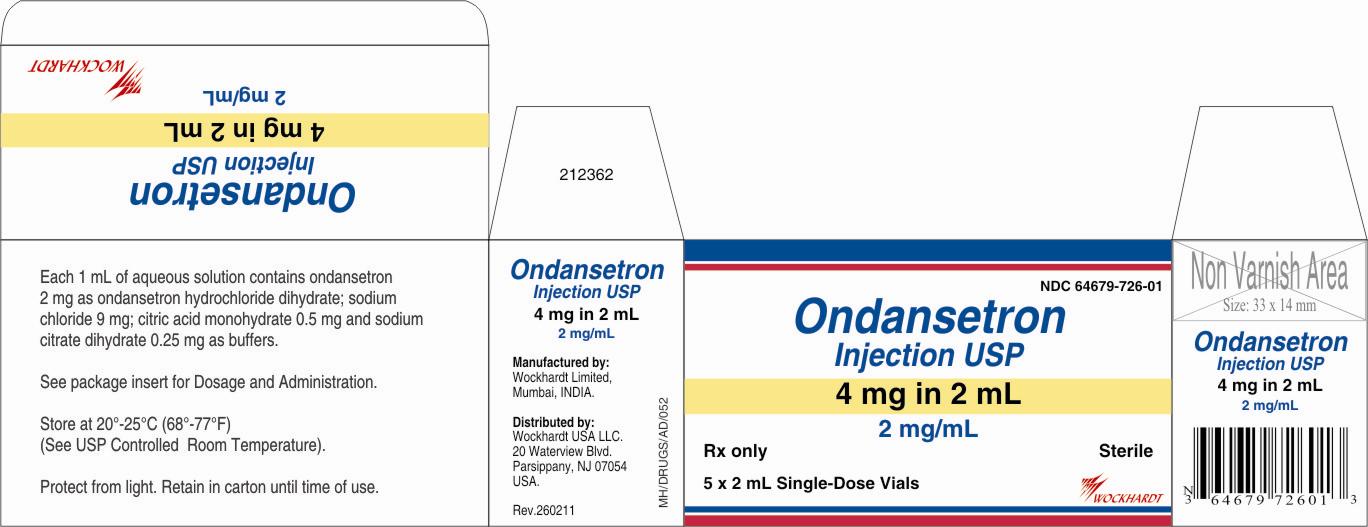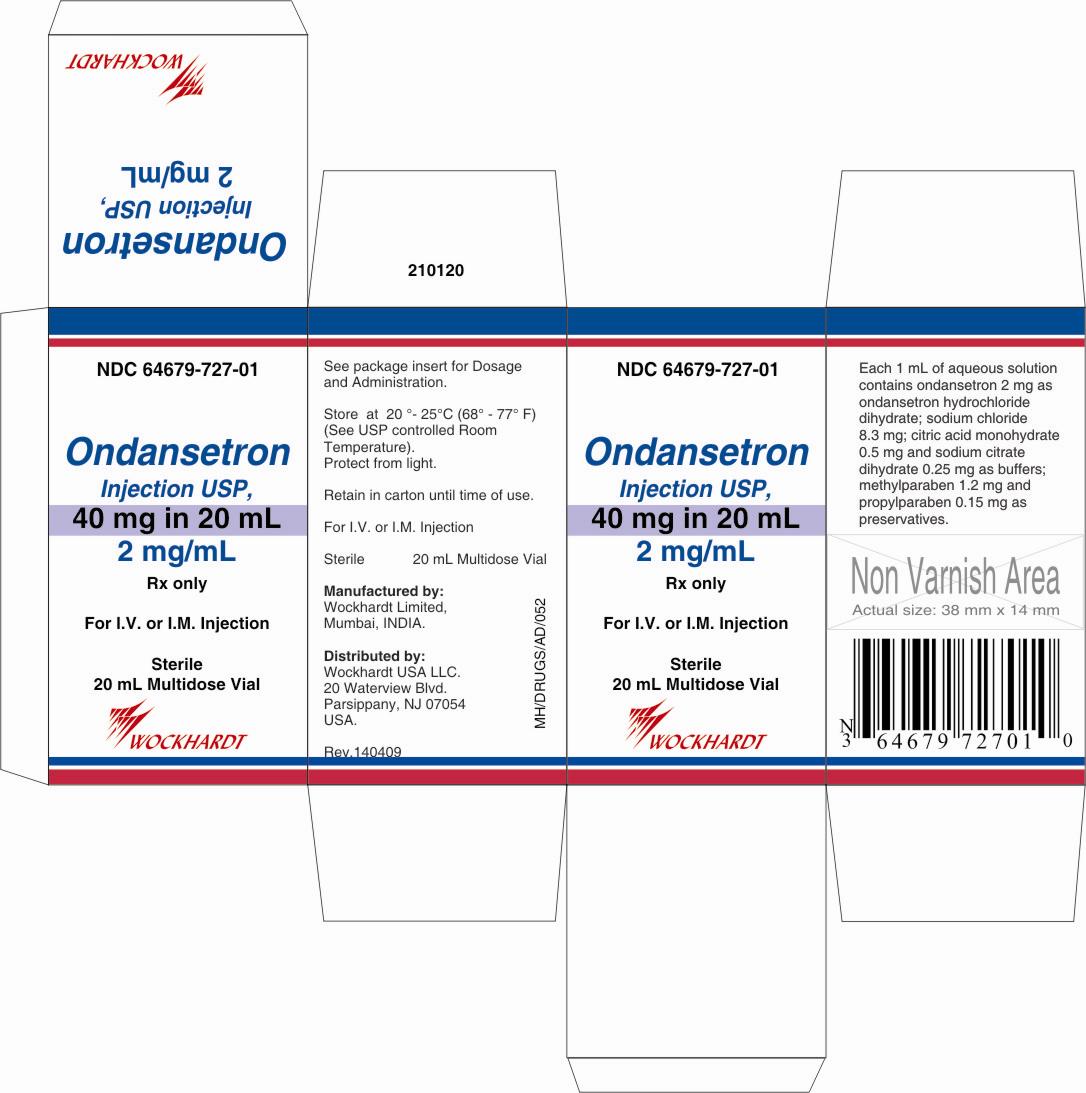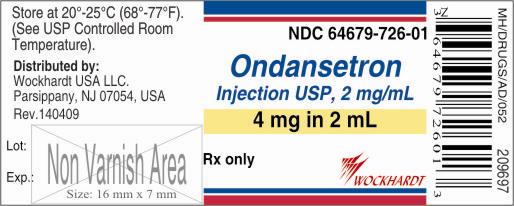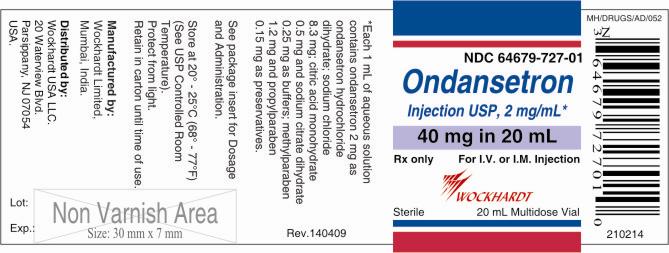 DRUG LABEL: ONDANSETRON HYDROCHLORIDE
NDC: 55648-726 | Form: INJECTION
Manufacturer: WOCKHARDT LIMITED
Category: prescription | Type: HUMAN PRESCRIPTION DRUG LABEL
Date: 20111129

ACTIVE INGREDIENTS: ONDANSETRON HYDROCHLORIDE 2 mg/1 mL
INACTIVE INGREDIENTS: SODIUM CHLORIDE; CITRIC ACID MONOHYDRATE; TRISODIUM CITRATE DIHYDRATE; WATER

PRESCRIBING INFORMATION
ONDANSETRON INJECTION USP

DESCRIPTION

The active ingredient in Ondansetron Injection is ondansetron hydrochloride (HCl), the racemic form of ondansetron and a selective blocking agent of the serotonin 5-HT3 receptor type. Chemically it is (±) 1, 2, 3, 9-tetrahydro-9-methyl-3-[(2-methyl-1H-imidazol-1-yl)methyl]-4H-carbazol-4-one, monohydrochloride, dihydrate. It has the following structural formula:

The empirical formula is C18H19N3O•HCl•2H2O, representing a molecular weight of 365.9.
Ondansetron HCl is a white to off-white powder that is soluble in water and normal saline.
Sterile Injection for Intravenous (I.V.) or Intramuscular (I.M.) Administration: Each 1 mL of aqueous solution in the 2-mL single-dose vial contains 2 mg of ondansetron as the hydrochloride dihydrate; 9 mg of sodium chloride, USP; and 0.5 mg of citric acid monohydrate, USP and 0.25 mg of sodium citrate dihydrate, USP as buffers in Water for Injection, USP.
Each 1 mL of aqueous solution in the 20-mL multidose vial contains 2 mg of ondansetron as the hydrochloride dihydrate; 8.3 mg of sodium chloride, USP; 0.5 mg of citric acid monohydrate, USP and 0.25 mg of sodium citrate dihydrate, USP as buffers; and 1.2 mg of methylparaben, NF and 0.15 mg of propylparaben, NF as preservatives in Water for Injection, USP.
Ondansetron Injection is a clear, colorless, nonpyrogenic, sterile solution. The pH of the injection solution is 3.3 to 4.0.

CLINICAL PHARMACOLOGY

Pharmacodynamics: Ondansetron is a selective 5-HT3 receptor antagonist. While ondansetron's mechanism of action has not been fully characterized, it is not a dopamine-receptor antagonist. Serotonin receptors of the 5-HT3 type are present both peripherally on vagal nerve terminals and centrally in the chemoreceptor trigger zone of the area postrema. It is not certain whether ondansetron's antiemetic action in chemotherapy-induced nausea and vomiting is mediated centrally, peripherally, or in both sites. However, cytotoxic chemotherapy appears to be associated with release of serotonin from the enterochromaffin cells of the small intestine. In humans, urinary 5-HIAA (5-hydroxyindoleacetic acid) excretion increases after cisplatin administration in parallel with the onset of vomiting. The released serotonin may stimulate the vagal afferents through the 5-HT3 receptors and initiate the vomiting reflex.
In animals, the emetic response to cisplatin can be prevented by pretreatment with an inhibitor of serotonin synthesis, bilateral abdominal vagotomy and greater splanchnic nerve section, or pretreatment with a serotonin 5-HT3 receptor antagonist.
In normal volunteers, single I.V. doses of 0.15 mg/kg of ondansetron had no effect on esophageal motility, gastric motility, lower esophageal sphincter pressure, or small intestinal transit time. In another study in six normal male volunteers, a 16-mg dose infused over 5 minutes showed no effect of the drug on cardiac output, heart rate, stroke volume, blood pressure, or electrocardiogram (ECG). Multiday administration of ondansetron has been shown to slow colonic transit in normal volunteers. Ondansetron has no effect on plasma prolactin concentrations.
In a gender-balanced pharmacodynamic study (n = 56), ondansetron 4 mg administered intravenously or intramuscularly was dynamically similar in the prevention of nausea and vomiting using the ipecacuanha model of emesis.
Ondansetron does not alter the respiratory depressant effects produced by alfentanil or the degree of neuromuscular blockade produced by atracurium. Interactions with general or local anesthetics have not been studied.
Pharmacokinetics: Ondansetron is extensively metabolized in humans, with approximately 5% of a radiolabeled dose recovered as the parent compound from the urine. The primary metabolic pathway is hydroxylation on the indole ring followed by glucuronide or sulfate conjugation.
Although some nonconjugated metabolites have pharmacologic activity, these are not found in plasma at concentrations likely to significantly contribute to the biological activity of ondansetron.
In vitro metabolism studies have shown that ondansetron is a substrate for human hepatic cytochrome P-450 enzymes, including CYP1A2, CYP2D6, and CYP3A4. In terms of overall ondansetron turnover, CYP3A4 played the predominant role. Because of the multiplicity of metabolic enzymes capable of metabolizing ondansetron, it is likely that inhibition or loss of one enzyme (e.g., CYP2D6 genetic deficiency) will be compensated by others and may result in little change in overall rates of ondansetron elimination. Ondansetron elimination may be affected by cytochrome P-450 inducers. In a pharmacokinetic study of 16 epileptic patients maintained chronically on CYP3A4 inducers, carbamazepine, or phenytoin, reduction in AUC, Cmax, and T½ of ondansetron was observed.^1 This resulted in a significant increase in clearance. However, on the basis of available data, no dosage adjustment for ondansetron is recommended (see PRECAUTIONS: Drug Interactions).
In humans, carmustine, etoposide, and cisplatin do not affect the pharmacokinetics of ondansetron.
In normal adult volunteers, the following mean pharmacokinetic data have been determined following a single 0.15-mg/kg I.V. dose.

Table 1. Pharmacokinetics in Normal Adult Volunteers
Age-group (years) | n | Peak Plasma Concentration (ng/mL) | Mean Elimination Half-life (h) | Plasma Clearance (L/h/kg)
19-40 | 11 | 102 | 3.5 | 0.381
61-74 | 12 | 106 | 4.7 | 0.319
≥75 | 11 | 170 | 5.5 | 0.262

A reduction in clearance and increase in elimination half-life are seen in patients over 75 years of age. In clinical trials with cancer patients, safety and efficacy were similar in patients over 65 years of age and those under 65 years of age; there was an insufficient number of patients over 75 years of age to permit conclusions in that age-group. No dosage adjustment is recommended in the elderly.
In patients with mild-to-moderate hepatic impairment, clearance is reduced 2-fold and mean half-life is increased to 11.6 hours compared to 5.7 hours in normals. In patients with severe hepatic impairment (Child-Pugh^2 score of 10 or greater), clearance is reduced 2-fold to 3-fold and apparent volume of distribution is increased with a resultant increase in half-life to 20 hours. In patients with severe hepatic impairment, a total daily dose of 8 mg should not be exceeded.
Due to the very small contribution (5%) of renal clearance to the overall clearance, renal impairment was not expected to significantly influence the total clearance of ondansetron. However, ondansetron mean plasma clearance was reduced by about 41% in patients with severe renal impairment (creatinine clearance <30 mL/min). This reduction in clearance is variable and was not consistent with an increase in half-life. No reduction in dose or dosing frequency in these patients is warranted.
In adult cancer patients, the mean elimination half-life was 4.0 hours, and there was no difference in the multidose pharmacokinetics over a 4-day period. In a study of 21 pediatric cancer patients (4 to 18 years of age) who received three I.V. doses of 0.15 mg/kg of ondansetron at 4-hour intervals, patients older than 15 years of age exhibited ondansetron pharmacokinetic parameters similar to those of adults. Patients 4 to 12 years of age generally showed higher clearance and somewhat larger volume of distribution than adults. Most pediatric patients younger than 15 years of age with cancer had a shorter (2.4 hours) ondansetron plasma half-life than patients older than 15 years of age. It is not known whether these differences in ondansetron plasma half-life may result in differences in efficacy between adults and some young pediatric patients (see CLINICAL TRIALS: Pediatric Studies).
Pharmacokinetic samples were collected from 74 cancer patients 6 to 48 months of age, who received a dose of 0.15 mg/kg of I.V. ondansetron every 4 hours for 3 doses during a safety and efficacy trial. These data were combined with sequential pharmacokinetics data from 41 surgery patients 1 month to 24 months of age, who received a single dose of 0.1 mg/kg of I.V. ondansetron prior to surgery with general anesthesia, and a population pharmacokinetic analysis was performed on the combined data set. The results of this analysis are included in Table 2 and are compared to the pharmacokinetic results in cancer patients 4 to 18 years of age.

Table 2. Pharmacokinetics in Pediatric Cancer Patients 1 Month to 18 Years of Age
Subjects and Age Group | N | CL; (L/h/kg) | Vdss; (L/kg) | T½; (h)
 |  | Geometric Mean |  | Mean
Pediatric Cancer Patients; 4 to 18 years of age | N = 21 | 0.599 | 1.9 | 2.8
Population PK Patientsa; 1 month to 48 months of age | N = 115 | 0.582 | 3.65 | 4.9

a Population PK (Pharmacokinetic) Patients: 64% cancer patients and 36% surgery patients.
Based on the population pharmacokinetic analysis, cancer patients 6 to 48 months of age who receive a dose of 0.15 mg/kg of I.V. ondansetron every 4 hours for 3 doses would be expected to achieve a systemic exposure (AUC) consistent with the exposure achieved in previous pediatric studies in cancer patients (4 to 18 years of age) at similar doses.
In a study of 21 pediatric patients (3 to 12 years of age) who were undergoing surgery requiring anesthesia for a duration of 45 minutes to 2 hours, a single I.V. dose of ondansetron, 2 mg (3 to 7 years) or 4 mg (8 to 12 years), was administered immediately prior to anesthesia induction. Mean weight-normalized clearance and volume of distribution values in these pediatric surgical patients were similar to those previously reported for young adults. Mean terminal half-life was slightly reduced in pediatric patients (range, 2.5 to 3 hours) in comparison with adults (range, 3 to 3.5 hours).
In a study of 51 pediatric patients (1 month to 24 months of age) who were undergoing surgery requiring general anesthesia, a single I.V. dose of ondansetron, 0.1 or 0.2 mg/kg, was administered prior to surgery. As shown in Table 3, the 41 patients with pharmacokinetic data were divided into 2 groups, patients 1 month to 4 months of age and patients 5 to 24 months of age, and are compared to pediatric patients 3 to 12 years of age.

Table 3. Pharmacokinetics in Pediatric Surgery Patients 1 Month to 12 Years of Age
Subjects and Age Group | N | CL (L/h/kg) | Vdss (L/kg) | T½ (h)
 |  | Geometric Mean |  | Mean
Pediatric Surgery Patients; 3 to 12 years of Age | N = 21 | 0.439 | 1.65 | 2.9
Pediatric Surgery Patients; 5 to 24 months of Age | N = 22 | 0.581 | 2.3 | 2.9
Pediatric Surgery Patients; 1 month to 4 months of Age | N = 19 | 0.401 | 3.5 | 6.7

In general, surgical and cancer pediatric patients younger than 18 years tend to have a higher ondansetron clearance compared to adults leading to a shorter half-life in most pediatric patients. In patients 1 month to 4 months of age, a longer half-life was observed due to the higher volume of distribution in this age group.
In normal volunteers (19 to 39 years old, n = 23), the peak plasma concentration was 264 ng/mL following a single 32-mg dose administered as a 15-minute I.V. infusion. The mean elimination half-life was 4.1 hours. Systemic exposure to 32 mg of ondansetron was not proportional to dose as measured by comparing dose-normalized AUC values to an 8-mg dose. This is consistent with a small decrease in systemic clearance with increasing plasma concentrations.
A study was performed in normal volunteers (n = 56) to evaluate the pharmacokinetics of a single 4-mg dose administered as a 5-minute infusion compared to a single intramuscular injection. Systemic exposure as measured by mean AUC was equivalent, with values of 156 [95% CI 136, 180] and 161 [95% CI 137, 190] ng•h/mL for I.V. and I.M. groups, respectively. Mean peak plasma concentrations were 42.9 [95% CI 33.8, 54.4] ng/mL at 10 minutes after I.V. infusion and 31.9 [95% CI 26.3, 38.6] ng/mL at 41 minutes after I.M. injection. The mean elimination half-life was not affected by route of administration.
Plasma protein binding of ondansetron as measured in vitro was 70% to 76%, with binding constant over the pharmacologic concentration range (10 to 500 ng/mL). Circulating drug also distributes into erythrocytes.
A positive lymphoblast transformation test to ondansetron has been reported, which suggests immunologic sensitivity to ondansetron.

CLINICAL TRIALS

Chemotherapy-Induced Nausea and Vomiting: Adult Studies: In a double-blind study of three different dosing regimens of ondansetron injection, 0.015 mg/kg, 0.15 mg/kg, and 0.30 mg/kg, each given three times during the course of cancer chemotherapy, the 0.15-mg/kg dosing regimen was more effective than the 0.015-mg/kg dosing regimen. The 0.30-mg/kg dosing regimen was not shown to be more effective than the 0.15-mg/kg dosing regimen.
Cisplatin-Based Chemotherapy: In a double-blind study in 28 patients, ondansetron injection (three 0.15-mg/kg doses) was significantly more effective than placebo in preventing nausea and vomiting induced by cisplatin-based chemotherapy. Treatment response was as shown in Table 4.

Table 4. Prevention of Chemotherapy-Induced Nausea and Vomiting in Single-Day Cisplatin Therapy* in Adults
 | Ondansetron Injection | Placebo | P Value†
Number of patients | 14 | 14
Treatment response
0 Emetic episodes | 2 (14%) | 0 (0%)
1-2 Emetic episodes | 8 (57%) | 0 (0%)
3-5 Emetic episodes | 2 (14%) | 1 (7%)
More than 5 emetic episodes/rescued | 2 (14%) | 13 (93%) | 0.001
Median number of emetic episodes | 1.5 | Undefined‡
Median time to first emetic episode (h) | 11.6 | 2.8 | 0.001
Median nausea scores (0-100)§ | 3 | 59 | 0.034
Global satisfaction with control of nausea and vomiting (0-100)II | 96 | 10.5 | 0.009

* Chemotherapy was high dose (100 and 120 mg/m^2; Ondansetron Injection n = 6, placebo n = 5) or moderate dose (50 and 80 mg/m^2; Ondansetron Injection n = 8, placebo n = 9). Other chemotherapeutic agents included fluorouracil, doxorubicin, and cyclophosphamide. There was no difference between treatments in the types of chemotherapy that would account for differences in response.
† Efficacy based on "all patients treated" analysis.
‡ Median undefined since at least 50% of the patients were rescued or had more than five emetic episodes.
§ Visual analog scale assessment of nausea: 0 = no nausea, 100 = nausea as bad as it can be.
II Visual analog scale assessment of satisfaction: 0 = not at all satisfied, 100 = totally satisfied.
Ondansetron was compared with metoclopramide in a single-blind trial in 307 patients receiving cisplatin ≥100 mg/m^2 with or without other chemotherapeutic agents. Patients received the first dose of ondansetron or metoclopramide 30 minutes before cisplatin. Two additional ondansetron doses were administered 4 and 8 hours later, or five additional metoclopramide doses were administered 2, 4, 7, 10, and 13 hours later. Cisplatin was administered over a period of 3 hours or less. Episodes of vomiting and retching were tabulated over the period of 24 hours after cisplatin. The results of this study are summarized in Table 5.

Table 5. Prevention of Vomiting Induced by Cisplatin (≥100 mg/m^2) Single-Day Therapy* in Adults
 | Ondansetron Injection | Metoclopramide | P Value
Dose | 0.15 mg/kg x 3 | 2 mg/kg x 6
Number of patients in efficacy population | 136 | 138
Treatment response
0 Emetic episodes | 54 (40%) | 41 (30%)
1-2 Emetic episodes | 34 (25%) | 30 (22%)
3-5 Emetic episodes | 19 (14%) | 18 (13%)
More than 5 emetic episodes/rescued | 29 (21%) | 49 (36%)
Comparison of treatments with respect to
0 Emetic episodes | 54/136 | 41/138 | 0.083
More than 5 emetic episodes/rescued | 29/136 | 49/138 | 0.009
Median number of emetic episodes | 1 | 2 | 0.005
Median time to first emetic episode (h) | 20.5 | 4.3 | <0.001
Global satisfaction with control of nausea and vomiting (0-100)† | 85 | 63 | 0.001
Acute dystonic reactions | 0 | 8 | 0.005
Akathisia | 0 | 10 | 0.002

* In addition to cisplatin, 68% of patients received other chemotherapeutic agents, including cyclophosphamide, etoposide, and fluorouracil. There was no difference between treatments in the types of chemotherapy that would account for differences in response.
† Visual analog scale assessment: 0 = not at all satisfied, 100 = totally satisfied.
In a stratified, randomized, double-blind, parallel-group, multicenter study, a single 32-mg dose of ondansetron was compared with three 0.15-mg/kg doses in patients receiving cisplatin doses of either 50 to 70 mg/m^2 or ≥100 mg/m^2. Patients received the first ondansetron dose 30 minutes before cisplatin. Two additional ondansetron doses were administered 4 and 8 hours later to the group receiving three 0.15-mg/kg doses. In both strata, significantly fewer patients on the single 32-mg dose than those receiving the three-dose regimen failed.

Table 6. Prevention of Chemotherapy-Induced Nausea and Vomiting in Single-Dose Therapy in Adults
 |  | Ondansetron Dose
 | 0.15 mg/kg x 3 | 32 mg x 1 | P Value
High-dose cisplatin (≥100 mg/m^2)
Number of patients | 100 | 102
Treatment response
0 Emetic episodes | 41 (41%) | 49 (48%) | 0.315
1-2 Emetic episodes | 19 (19%) | 25 (25%)
3-5 Emetic episodes | 4 (4%) | 8 (8%)
More than 5 emetic episodes/rescued | 36 (36%) | 20 (20%) | 0.009
Median time to first emetic episode (h) | 21.7 | 23 | 0.173
Median nausea scores (0-100)* | 28 | 13 | 0.004
Medium-dose cisplatin (50-70 mg/m^2)
Number of patients | 101 | 93
Treatment response
0 Emetic episodes | 62 (61%) | 68 (73%) | 0.083
1-2 Emetic episodes | 11 (11%) | 14 (15%)
3-5 Emetic episodes | 6 (6%) | 3 (3%)
More than 5 emetic episodes/rescued | 22 (22%) | 8 (9%) | 0.011
Median time to first emetic episode (h) | Undefined† | Undefined
Median nausea scores (0-100)* | 9 | 3 | 0.131

* Visual analog scale assessment: 0 = no nausea, 100 = nausea as bad as it can be.
† Median undefined since at least 50% of patients did not have any emetic episodes.
Cyclophosphamide-Based Chemotherapy: In a double-blind, placebo-controlled study of ondansetron injection (three 0.15-mg/kg doses) in 20 patients receiving cyclophosphamide (500 to 600 mg/m^2) chemotherapy, ondansetron injection was significantly more effective than placebo in preventing nausea and vomiting. The results are summarized in Table 7.

Table 7. Prevention of Chemotherapy-Induced Nausea and Vomiting in Single-Day Cyclophosphamide Therapy* in Adults
 | Ondansetron Injection | Placebo | P Value†
Number of patients | 10 | 10
Treatment response
0 Emetic episodes | 7 (70%) | 0 (0%) | 0.001
1-2 Emetic episodes | 0 (0%) | 2 (20%)
3-5 Emetic episodes | 2 (20%) | 4 (40%)
More than 5 emetic episodes/rescued | 1 (10%) | 4 (40%) | 0.131
Median number of emetic episodes | 0 | 4 | 0.008
Median time to first emetic episode (h) | Undefined‡ | 8.79
Median nausea scores (0-100)§ | 0 | 60 | 0.001
Global satisfaction with control of nausea and vomiting (0-100)II | 100 | 52 | 0.008

* Chemotherapy consisted of cyclophosphamide in all patients, plus other agents, including fluorouracil, doxorubicin, methotrexate, and vincristine. There was no difference between treatments in the type of chemotherapy that would account for differences in response.
† Efficacy based on "all patients treated" analysis.
‡ Median undefined since at least 50% of patients did not have any emetic episodes.
§ Visual analog scale assessment of nausea: 0 = no nausea, 100 = nausea as bad as it can be.
II Visual analog scale assessment of satisfaction: 0 = not at all satisfied, 100 = totally satisfied.
Re-treatment: In uncontrolled trials, 127 patients receiving cisplatin (median dose, 100 mg/m^2) and ondansetron who had two or fewer emetic episodes were re-treated with ondansetron and chemotherapy, mainly cisplatin, for a total of 269 re-treatment courses (median, 2; range, 1 to 10). No emetic episodes occurred in 160 (59%), and two or fewer emetic episodes occurred in 217 (81%) re-treatment courses.
Pediatric Studies: Four open-label, noncomparative (one US, three foreign) trials have been performed with 209 pediatric cancer patients 4 to 18 years of age given a variety of cisplatin or noncisplatin regimens. In the three foreign trials, the initial ondansetron injection dose ranged from 0.04 to 0.87 mg/kg for a total dose of 2.16 to 12 mg. This was followed by the oral administration of ondansetron ranging from 4 to 24 mg daily for 3 days. In the US trial, ondansetron was administered intravenously (only) in three doses of 0.15 mg/kg each for a total daily dose of 7.2 to 39 mg. In these studies, 58% of the 196 evaluable patients had a complete response (no emetic episodes) on day 1. Thus, prevention of vomiting in these pediatric patients was essentially the same as for patients older than 18 years of age.
An open-label, multicenter, noncomparative trial has been performed in 75 pediatric cancer patients 6 to 48 months of age receiving at least one moderately or highly emetogenic chemotherapeutic agent. Fifty-seven percent (57%) were females; 67% were white, 18% were American Hispanic, and 15% were black patients. Ondansetron injection was administered intravenously over 15 minutes in three doses of 0.15 mg/kg. The first dose was administered 30 minutes before the start of chemotherapy, the second and third doses were administered 4 and 8 hours after the first dose, respectively. Eighteen patients (25%) received routine prophylactic dexamethasone (i.e., not given as rescue). Of the 75 evaluable patients, 56% had a complete response (no emetic episodes) on day 1. Thus, prevention of vomiting in these pediatric patients was comparable to the prevention of vomiting in patients 4 years of age and older.
Postoperative Nausea and Vomiting: Prevention of Postoperative Nausea and Vomiting: Adult Studies: Adult surgical patients who received ondansetron immediately before the induction of general balanced anesthesia (barbiturate: thiopental, methohexital, or thiamylal; opioid: alfentanil or fentanyl; nitrous oxide; neuromuscular blockade: succinylcholine/curare and/or vecuronium or atracurium; and supplemental isoflurane) were evaluated in two double-blind US studies involving 554 patients. Ondansetron injection (4 mg) I.V. given over 2 to 5 minutes was significantly more effective than placebo. The results of these studies are summarized in Table 8.

Table 8. Prevention of Postoperative Nausea and Vomiting in Adult Patients
 | Ondansetron 4 mg I.V. | Placebo | P Value
Study 1
Emetic episodes:
Number of patients | 136 | 139
Treatment response over 24-h postoperative period
0 Emetic episodes | 103 (76%) | 64 (46%) | <0.001
1 Emetic episode | 13 (10%) | 17 (12%)
More than 1 emetic episode/rescued | 20 (15%) | 58 (42%)
Nausea assessments:
Number of patients | 134 | 136
No nausea over 24-h postoperative period | 56 (42%) | 39 (29%)
Study 2
Emetic episodes:
Number of patients | 136 | 143
Treatment response over 24-h postoperative period
0 Emetic episodes | 85 (63%) | 63 (44%) | 0.002
1 Emetic episode | 16 (12%) | 29 (20%)
More than 1 emetic episode/rescued | 35 (26%) | 51 (36%)
Nausea assessments:
Number of patients | 125 | 133
No nausea over 24-h postoperative period | 48 (38%) | 42 (32%)

The study populations in Table 8 consisted mainly of females undergoing laparoscopic procedures.
In a placebo-controlled study conducted in 468 males undergoing outpatient procedures, a single 4-mg I.V. ondansetron dose prevented postoperative vomiting over a 24-hour study period in 79% of males receiving drug compared to 63% of males receiving placebo (P <0.001).
Two other placebo-controlled studies were conducted in 2,792 patients undergoing major abdominal or gynecological surgeries to evaluate a single 4-mg or 8-mg I.V. ondansetron dose for prevention of postoperative nausea and vomiting over a 24-hour study period. At the 4-mg dosage, 59% of patients receiving ondansetron versus 45% receiving placebo in the first study (P < 0.001) and 41% of patients receiving ondansetron versus 30% receiving placebo in the second study (P=0.001) experienced no emetic episodes. No additional benefit was observed in patients who received I.V. ondansetron 8 mg compared to patients who received I.V. ondansetron 4 mg.
Pediatric Studies: Three double-blind, placebo-controlled studies have been performed (one US, two foreign) in 1,049 male and female patients (2 to 12 years of age) undergoing general anesthesia with nitrous oxide. The surgical procedures included tonsillectomy with or without adenoidectomy, strabismus surgery, herniorrhaphy, and orchidopexy. Patients were randomized to either single I.V. doses of ondansetron (0.1 mg/kg for pediatric patients weighing 40 kg or less, 4 mg for pediatric patients weighing more than 40 kg) or placebo. Study drug was administered over at least 30 seconds, immediately prior to or following anesthesia induction. Ondansetron was significantly more effective than placebo in preventing nausea and vomiting. The results of these studies are summarized in Table 9.

Table 9. Prevention of Postoperative Nausea and Vomiting in Pediatric Patients 2 to 12 Years of Age
Treatment Response Over 24 Hours | Ondansetron n (%) | Placebo n (%) | P Value
Study 1
Number of patients | 205 | 210
0 Emetic episodes | 140 (68%) | 82 (39%) | ≤0.001
Failure* | 65 (32%) | 128 (61%)
Study 2
Number of patients | 112 | 110
0 Emetic episodes | 68 (61%) | 38 (35%) | ≤0.001
Failure* | 44 (39%) | 72 (65%)
Study 3
Number of patients | 206 | 206
0 Emetic episodes | 123 (60%) | 96 (47%) | ≤0.01
Failure* | 83 (40%) | 110 (53%)
Nausea assessments†:
Number of patients | 185 | 191
None | 119 (64%) | 99 (52%) | ≤0.01

* Failure was one or more emetic episodes, rescued, or withdrawn.
† Nausea measured as none, mild, or severe.
A double-blind, multicenter, placebo-controlled study was conducted in 670 pediatric patients 1 month to 24 months of age who were undergoing routine surgery under general anesthesia.
Seventy-five percent (75%) were males; 64% were white, 15% were black, 13% were American Hispanic, 2% were Asian, and 6% were "other race" patients. A single 0.1-mg/kg I.V. dose of ondansetron administered within 5 minutes following induction of anesthesia was statistically significantly more effective than placebo in preventing vomiting. In the placebo group, 28% of patients experienced vomiting compared to 11% of subjects who received ondansetron (P≤ 0.01). Overall, 32 (10%) of placebo patients and 18 (5%) of patients who received ondansetron received antiemetic rescue medication(s) or prematurely withdrew from the study.
Prevention of Further Postoperative Nausea and Vomiting: Adult Studies: Adult surgical patients receiving general balanced anesthesia (barbiturate: thiopental, methohexital, or thiamylal; opioid: alfentanil or fentanyl; nitrous oxide; neuromuscular blockade: succinylcholine/curare and/or vecuronium or atracurium; and supplemental isoflurane) who received no prophylactic antiemetics and who experienced nausea and/or vomiting within 2 hours postoperatively were evaluated in two double-blind US studies involving 441 patients. Patients who experienced an episode of postoperative nausea and/or vomiting were given Ondansetron Injection (4 mg) I.V. over 2 to 5 minutes, and this was significantly more effective than placebo. The results of these studies are summarized in Table 10.

Table 10. Prevention of Further Postoperative Nausea and Vomiting in Adult Patients
 | Ondansetron 4 mg I.V. | Placebo | P Value
Study 1
Emetic episodes:
Number of patients | 104 | 117
Treatment response 24 h after study drug
0 Emetic episodes | 49 (47%) | 19 (16%) | <0.001
1 Emetic episode | 12 (12%) | 9 (8%)
More than 1 emetic episode/rescued | 43 (41%) | 89 (76%)
Median time to first emetic episode (min)* | 55.0 | 43.0
Nausea assessments:
Number of patients | 98 | 102
Mean nausea score over 24-hpostoperative period† | 1.7 | 3.1
Study 2
Emetic episodes:
Number of patients | 112 | 108
Treatment response 24 h after study drug
0 Emetic episodes | 49 (44%) | 28 (26%) | 0.006
1 Emetic episode | 14 (13%) | 3 (3%)
More than 1 emetic episode/rescued | 49 (44%) | 77 (71%)
Median time to first emetic episode (min)* | 60.5 | 34.0
Nausea assessments:
Number of patients | 105 | 85
Mean nausea score over 24-hpostoperative period† | 1.9 | 2.9

* After administration of study drug.
† Nausea measured on a scale of 0-10 with 0 = no nausea, 10 = nausea as bad as it can be.
The study populations in Table 9 consisted mainly of women undergoing laparoscopic procedures.
Repeat Dosing in Adults: In patients who do not achieve adequate control of postoperative nausea and vomiting following a single, prophylactic, preinduction, I.V. dose of ondansetron 4 mg, administration of a second I.V. dose of ondansetron 4 mg postoperatively does not provide additional control of nausea and vomiting.
Pediatric Study: One double-blind, placebo-controlled, US study was performed in 351 male and female outpatients (2 to 12 years of age) who received general anesthesia with nitrous oxide and no prophylactic antiemetics. Surgical procedures were unrestricted. Patients who experienced two or more emetic episodes within 2 hours following discontinuation of nitrous oxide were randomized to either single I.V. doses of ondansetron (0.1 mg/kg for pediatric patients weighing 40 kg or less, 4 mg for pediatric patients weighing more than 40 kg) or placebo administered over at least 30 seconds. Ondansetron was significantly more effective than placebo in preventing further episodes of nausea and vomiting. The results of the study are summarized in Table 11.

Table 11. Prevention of Further Postoperative Nausea and Vomiting in Pediatric Patients 2 to 12 Years of Age
Treatment Response Over 24 Hours | Ondansetron n (%) | Placebo n (%) | P Value
Number of patients | 180 | 171
0 Emetic episodes | 96 (53%) | 29 (17%) | ≤0.001
Failure* | 84 (47%) | 142 (83%)

* Failure was one or more emetic episodes, rescued, or withdrawn.

INDICATIONS AND USAGE

1. Prevention of nausea and vomiting associated with initial and repeat courses of emetogenic cancer chemotherapy, including high-dose cisplatin. Efficacy of the 32-mg single dose beyond 24 hours in these patients has not been established.
2. Prevention of postoperative nausea and/or vomiting. As with other antiemetics, routine prophylaxis is not recommended for patients in whom there is little expectation that nausea and/or vomiting will occur postoperatively. In patients where nausea and/or vomiting must be avoided postoperatively, ondansetron injection is recommended even where the incidence of postoperative nausea and/or vomiting is low. For patients who do not receive prophylactic ondansetron injection and experience nausea and/or vomiting postoperatively, ondansetron injection may be given to prevent further episodes (see CLINICAL TRIALS).

CONTRAINDICATIONS

The concomitant use of apomorphine with ondansetron is contraindicated based on reports of profound hypotension and loss of consciousness when apomorphine was administered with ondansetron.
Ondansetron injection is contraindicated for patients known to have hypersensitivity to the drug.

WARNINGS

Hypersensitivity reactions have been reported in patients who have exhibited hypersensitivity to other selective 5-HT3 receptor antagonists.

PRECAUTIONS

General: Ondansetron is not a drug that stimulates gastric or intestinal peristalsis. It should not be used instead of nasogastric suction. The use of ondansetron in patients following abdominal surgery or in patients with chemotherapy-induced nausea and vomiting may mask a progressive ileus and/or gastric distention.
Rarely and predominantly with intravenous ondansetron, transient ECG changes including QT interval prolongation have been reported.
Drug Interactions: Ondansetron does not itself appear to induce or inhibit the cytochrome P-450 drug-metabolizing enzyme system of the liver (See CLINICAL PHARMACOLOGY: Pharmacokinetics). Because ondansetron is metabolized by hepatic cytochrome P-450 drug-metabolizing enzymes (CYP3A4, CYP2D6, CYP1A2), inducers or inhibitors of these enzymes may change the clearance and, hence, the half-life of ondansetron. On the basis of limited available data, no dosage adjustment is recommended for patients on these drugs.
Apomorphine: Based on reports of profound hypotension and loss of consciousness when apomorphine was administered with ondansetron, concomitant use of apomorphine with ondansetron is contraindicated (see CONTRAINDICATIONS).
Phenytoin, Carbamazepine, and Rifampicin: In patients treated with potent inducers of CYP3A4 (i.e., phenytoin, carbamazepine, and rifampicin), the clearance of ondansetron was significantly increased and ondansetron blood concentrations were decreased. However, on the basis of available data, no dosage adjustment for ondansetron is recommended for patients on these drugs. ^1,3
Tramadol: Although no pharmacokinetic drug interaction between ondansetron and tramadol has been observed, data from 2 small studies indicate that ondansetron may be associated with an increase in patient controlled administration of tramadol.^4,5
Chemotherapy: Tumor response to chemotherapy in the P 388 mouse leukemia model is not affected by ondensetron. In humans, carmustine, etoposide, and cisplatin do not affect the pharmacokinetics of ondansetron.
In a crossover study in 76 pediatric patients, I.V. ondansetron did not increase blood levels of high-dose methotrexate.
Carcinogenesis, Mutagenesis, Impairment of Fertility: Carcinogenic effects were not seen in 2-year studies in rats and mice with oral ondansetron doses up to 10 and 30 mg/kg per day, respectively. Ondansetron was not mutagenic in standard tests for mutagenicity. Oral administration of ondansetron up to 15 mg/kg per day did not affect fertility or general reproductive performance of male and female rats.
Pregnancy: Teratogenic Effects: Pregnancy Category B. Reproduction studies have been performed in pregnant rats and rabbits at I.V. doses up to 4 mg/kg per day and have revealed no evidence of impaired fertility or harm to the fetus due to ondansetron. There are, however, no adequate and well-controlled studies in pregnant women. Because animal reproduction studies are not always predictive of human response, this drug should be used during pregnancy only if clearly needed.
Nursing Mothers: Ondansetron is excreted in the breast milk of rats. It is not known whether ondansetron is excreted in human milk. Because many drugs are excreted in human milk, caution should be exercised when ondansetron is administered to a nursing woman.
Pediatric Use: Little information is available about the use of ondansetron in pediatric surgical patients younger than 1 month of age. (See CLINICAL TRIALS section for studies of ondansetron in prevention of postoperative nausea and vomiting in patients 1 month of age and older.) Little information is available about the use of ondansetron in pediatric cancer patients younger than 6 months of age. (See CLINICAL TRIALS section for studies of ondansetron in chemotherapy-induced nausea and vomiting in pediatric patients 6 months of age and older.) (See DOSAGE AND ADMINISTRATION.)
The clearance of ondansetron in pediatric patients 1 month to 4 months of age is slower and the half-life is ~2.5 fold longer than patients who are >4 to 24 months of age. As a precaution, it is recommended that patients less than 4 months of age receiving this drug be closely monitored. (See CLINICAL PHARMACOLOGY: Pharmacokinetics).
The frequency and type of adverse events reported in pediatric patients receiving ondansetron were similar to those in patients receiving placebo.(See ADVERSE EVENTS.)
Geriatric Use: Of the total number of subjects enrolled in cancer chemotherapy-induced and postoperative nausea and vomiting in US- and foreign-controlled clinical trials, 862 were 65 years of age and over. No overall differences in safety or effectiveness were observed between these subjects and younger subjects, and other reported clinical experience has not identified differences in responses between the elderly and younger patients, but greater sensitivity of some older individuals cannot be ruled out. Dosage adjustment is not needed in patients over the age of 65 (see CLINICAL PHARMACOLOGY).

ADVERSE REACTIONS

Chemotherapy-Induced Nausea and Vomiting: The adverse events in Table 12 have been reported in adults receiving ondansetron at a dosage of three 0.15-mg/kg doses or as a single 32-mg dose in clinical trials. These patients were receiving concomitant chemotherapy, primarily cisplatin, and IV. fluids. Most were receiving a diuretic.

Table 12. Principal Adverse Events in Comparative Trials in Adults
 | Number of Adult Patients With Event
 | Ondansetron Injection; 0.15 mg/kg x 3; n = 419 | Ondansetron Injection; 32 mg x 1; n = 220 | Metoclopramide; n = 156 | Placebo; n = 34
Diarrhea | 16% | 8% | 44% | 18%
Headache | 17% | 25% | 7% | 15%
Fever | 8% | 7% | 5% | 3%
Akathisia | 0% | 0% | 6% | 0%
Acute dystonic reactions* | 0% | 0% | 5% | 0%

* See Neurological.
The following have been reported during controlled clinical trials:
Cardiovascular: Rare cases of angina (chest pain), electrocardiographic alterations, hypotension, and tachycardia have been reported. In many cases, the relationship to ondansetron injection was unclear.
Gastrointestinal: Constipation has been reported in 11% of chemotherapy patients receiving multiday ondansetron.
Hepatic: In comparative trials in cisplatin chemotherapy patients with normal baseline values of aspartate transaminase (AST) and alanine transaminase (ALT), these enzymes have been reported to exceed twice the upper limit of normal in approximately 5% of patients. The increases were transient and did not appear to be related to dose or duration of therapy. On repeat exposure, similar transient elevations in transaminase values occurred in some courses, but symptomatic hepatic disease did not occur.
Integumentary: Rash has occurred in approximately 1% of patients receiving ondansetron.
Neurological: There have been rare reports consistent with, but not diagnostic of, extrapyramidal reactions in patients receiving ondansetron injection, and rare cases of grand mal seizure. The relationship to ondansetron was unclear.
Other: Rare cases of hypokalemia have been reported. The relationship to ondansetron injection was unclear.
Postoperative Nausea and Vomiting: The adverse events in Table 13 have been reported in ≥2% of adults receiving ondansetron at a dosage of 4 mg I.V. over 2 to 5 minutes in clinical trials. Rates of these events were not significantly different in the ondansetron and placebo groups. These patients were receiving multiple concomitant perioperative and postoperative medications.

Table 13. Adverse Events in ≥ 2% of Adults Receiving Ondansetron at a Dosage of 4 mg I.V. over 2 to 5 Minutes in Clinical Trials
 | Ondansetron Injection; 4 mg I.V.; n = 547 patients | Placebo; n = 547 patients
Headache | 92 (17%) | 77 (14%)
Dizziness | 67 (12%) | 88 (16%)
Musculoskeletal pain | 57 (10%) | 59 (11%)
Drowsiness/sedation | 44 (8%) | 37 (7%)
Shivers | 38 (7%) | 39 (7%)
Malaise/fatigue | 25 (5%) | 30 (5%)
Injection site reaction | 21 (4%) | 18 (3%)
Urinary retention | 17 (3%) | 15 (3%)
Postoperative CO2-related pain* | 12 (2%) | 16 (3%)
Chest pain (unspecified) | 12 (2%) | 15 (3%)
Anxiety/agitation | 11 (2%) | 16 (3%)
Dysuria | 11 (2%) | 9 (2%)
Hypotension | 10 (2%) | 12 (2%)
Fever | 10 (2%) | 6 (1%)
Cold sensation | 9 (2%) | 8 (1%)
Pruritus | 9 (2%) | 3 (<1%)
Paresthesia | 9 (2%) | 2 (<1%)

* Sites of pain included abdomen, stomach, joints, rib cage, shoulder.
Pediatric Use: The adverse events in Table 14 were the most commonly reported adverse events in pediatric patients receiving ondansetron (a single 0.1-mg/kg dose for pediatric patients weighing 40 kg or less, or 4 mg for pediatric patients weighing more than 40 kg) administered intravenously over at least 30 seconds. Rates of these events were not significantly different in the ondansetron and placebo groups. These patients were receiving multiple concomitant perioperative and postoperative medications.

Table 14. Frequency of Adverse Events From Controlled Studies in Pediatric Patients 2 to 12 Years of Age
Adverse Event | Ondansetron; n = 755 Patients | Placebo; n = 731 Patients
Wound problem | 80 (11%) | 86 (12%)
Anxiety/agitation | 49 (6%) | 47 (6%)
Headache | 44 (6%) | 43 (6%)
Drowsiness/sedation | 41 (5%) | 56 (8%)
Pyrexia | 32 (4%) | 41 (6%)

The adverse events in Table 15 were the most commonly reported adverse events in pediatric patients, 1 month to 24 months of age, receiving a single 0.1-mg/kg I.V. dose of ondansetron. The incidence and type of adverse events were similar in both the ondansetron and placebo groups. These patients were receiving multiple concomitant perioperative and postoperative medications.

Table 15. Frequency of Adverse Events (Greater Than or Equal to 2% in Either Treatment Group) in Pediatric Patients 1 Month to 24 Months of Age
Adverse Event | Ondansetron; n = 336 Patients | Placebo; n = 334 Patients
Pyrexia | 14 (4%) | 14 (4%)
Bronchospasm | 2 (< 1%) | 6 (2%)
Post-procedural pain | 4 (1%) | 6 (2%)
Diarrhea | 6 (2%) | 3 (< 1%)

Observed During Clinical Practice: In addition to adverse events reported from clinical trials, the following events have been identified during post-approval use of intravenous formulations of ondansetron. Because they are reported voluntarily from a population of unknown size, estimates of frequency cannot be made. The events have been chosen for inclusion due to a combination of their seriousness, frequency of reporting, or potential causal connection to ondansetron.
Cardiovascular: Arrhythmias (including ventricular and supraventricular tachycardia, premature ventricular contractions, and atrial fibrillation), bradycardia, electrocardiographic alterations (including second-degree heart block, QT interval prolongation, and ST segment depression), palpitations, and syncope.
General: Flushing. Rare cases of hypersensitivity reactions, sometimes severe (e.g., anaphylaxis/anaphylactoid reactions, angioedema, bronchospasm, cardiopulmonary arrest, hypotension, laryngeal edema, laryngospasm, shock, shortness of breath, stridor) have also been reported.
Hepatobiliary: Liver enzyme abnormalities have been reported. Liver failure and death have been reported in patients with cancer receiving concurrent medications including potentially hepatotoxic cytotoxic chemotherapy and antibiotics. The etiology of the liver failure is unclear.
Local Reactions: Pain, redness, and burning at site of injection.
Lower Respiratory: Hiccups
Neurological: Oculogyric crisis, appearing alone, as well as with other dystonic reactions.
Skin: Urticaria
Special Senses: Transient dizziness during or shortly after I.V. infusion.
Eye Disorders: Transient blurred vision, in some cases associated with abnormalities of accommodation. Cases of transient blindness, predominantly during intravenous administration, have been reported. These cases of transient blindness were reported to resolve within a few minutes up to 48 hours.

DRUG ABUSE AND DEPENDENCE

Animal studies have shown that ondansetron is not discriminated as a benzodiazepine nor does it substitute for benzodiazepines in direct addiction studies.

OVERDOSAGE

There is no specific antidote for ondansetron overdose. Patients should be managed with appropriate supportive therapy. Individual doses as large as 150 mg and total daily dosages (three doses) as large as 252 mg have been administered intravenously without significant adverse events. These doses are more than 10 times the recommended daily dose.
In addition to the adverse events listed above, the following events have been described in the setting of ondansetron overdose: "Sudden blindness" (amaurosis) of 2 to 3 minutes' duration plus severe constipation occurred in one patient that was administered 72 mg of ondansetron intravenously as a single dose. Hypotension (and faintness) occurred in another patient that took 48 mg of oral ondansetron. Following infusion of 32 mg over only a 4-minute period, a vasovagal episode with transient second-degree heart block was observed. In all instances, the events resolved completely.

DOSAGE AND ADMINISTRATION

Prevention of Chemotherapy-Induced Nausea and Vomiting: Adult Dosing: The recommended I.V. dosage of ondansetron for adults is a single 32-mg dose or three 0.15-mg/kg doses. A single 32-mg dose is infused over 15 minutes beginning 30 minutes before the start of emetogenic chemotherapy. The recommended infusion rate should not be exceeded (see OVERDOSAGE). With the three-dose (0.15-mg/kg) regimen, the first dose is infused over 15 minutes beginning 30 minutes before the start of emetogenic chemotherapy. Subsequent doses (0.15 mg/kg) are administered 4 and 8 hours after the first dose of ondansetron.
Ondansetron injection should not be mixed with solutions for which physical and chemical compatibility have not been established. In particular, this applies to alkaline solutions as a precipitate may form.
Vial: DILUTE BEFORE USE FOR PREVENTION OF CHEMOTHERAPY-INDUCED NAUSEA AND VOMITING. Ondansetron injection should be diluted in 50 mL of 5% Dextrose Injection or 0.9% Sodium Chloride Injection before administration.
Pediatric Dosing: On the basis of the available information (see CLINICAL TRIALS: Pediatric Studies and CLINICAL PHARMACOLOGY: Pharmacokinetics), the dosage in pediatric cancer patients 6 months to 18 years of age should be three 0.15-mg/kg doses. The first dose is to be administered 30 minutes before the start of moderately to highly emetogenic chemotherapy, subsequent doses (0.15 mg/kg) are administered 4 and 8 hours after the first dose of ondansetron. The drug should be infused intravenously over 15 minutes. Little information is available about dosage in pediatric cancer patients younger than 6 months of age.
Vial: DILUTE BEFORE USE FOR PREVENTION OF CHEMOTHERAPY-INDUCED NAUSEA AND VOMITING. Ondansetron injection should be diluted in 50 mL of 5% Dextrose Injection or 0.9% Sodium Chloride Injection before administration.
Geriatric Dosing: The dosage recommendation is the same as for the general population.
Prevention of Postoperative Nausea and Vomiting: Adult Dosing: The recommended I.V. dosage of ondansetron for adults is 4 mg undiluted administered intravenously in not less than 30 seconds, preferably over 2 to 5 minutes, immediately before induction of anesthesia, or postoperatively if the patient experiences nausea and/or vomiting occurring shortly after surgery. Alternatively, 4 mg undiluted may be administered intramuscularly as a single injection for adults. While recommended as a fixed dose for patients weighing more than 40 kg, few patients above 80 kg have been studied. In patients who do not achieve adequate control of postoperative nausea and vomiting following a single, prophylactic, preinduction, I.V. dose of ondansetron 4 mg, administration of a second I.V. dose of 4 mg ondansetron postoperatively does not provide additional control of nausea and vomiting.
Vial: REQUIRES NO DILUTION FOR ADMINISTRATION FOR POSTOPERATIVE NAUSEA AND VOMITING.
Pediatric Dosing: The recommended I.V. dosage of ondansetron for pediatric surgical patients (1 month to 12 years of age) is a single 0.1-mg/kg dose for patients weighing 40 kg or less, or a single 4-mg dose for patients weighing more than 40 kg. The rate of administration should not be less than 30 seconds, preferably over 2 to 5 minutes immediately prior to or following anesthesia induction, or postoperatively if the patient experiences nausea and/or vomiting occurring shortly after surgery. Prevention of further nausea and vomiting was only studied in patients who had not received prophylactic ondansetron.
Vial: REQUIRES NO DILUTION FOR ADMINISTRATION FOR POSTOPERATIVE NAUSEA AND VOMITING.
Geriatric Dosing: The dosage recommendation is the same as for the general population.
Dosage Adjustment for Patients With Impaired Renal Function: The dosage recommendation is the same as for the general population. There is no experience beyond first-day administration of ondansetron.
Dosage Adjustment for Patients With Impaired Hepatic Function: In patients with severe hepatic impairment (Child-Pugh2 score of 10 or greater), a single maximal daily dose of 8 mg to be infused over 15 minutes beginning 30 minutes before the start of the emetogenic chemotherapy is recommended. There is no experience beyond first-day administration of ondansetron.
Stability: Ondansetron injection is stable at room temperature under normal lighting conditions for 48 hours after dilution with the following I.V. fluids: 0.9% Sodium Chloride Injection, 5% Dextrose Injection, 5% Dextrose and 0.9% Sodium Chloride Injection, 5% Dextrose and 0.45% Sodium Chloride Injection, and 3% Sodium Chloride Injection.
Although odansetron injection is chemically and physically stable when diluted as recommended, sterile precautions should be observed because diluents generally do not contain preservative. After dilution, do not use beyond 24 hours.
Note: Parenteral drug products should be inspected visually for particulate matter and discoloration before administration whenever solution and container permit.
Precaution: Occasionally, ondansetron precipitates at the stopper/vial interface in vials stored upright. Potency and safety are not affected. If a precipitate is observed, resolubilize by shaking the vial vigorously.

HOW SUPPLIED

Ondansetron Injection, 2 mg/mL, is supplied as follows:
NDC 64679-726-01 2-mL single-dose vials (Carton of 5)
NDC 64679-727-01 20-mL multidose vials (Singles)
Store at 20°-25°C (68°-77°F) (See USP Controlled Room Temperature). Protect from light.
Retain in carton until time of use.
REFERENCES

1. Britto MR, Hussey EK, Mydlow P, et al. Effect of enzyme inducers on ondansetron (OND) metabolism in humans. Clin Pharmacol Ther. 1997;61:228.
2. Pugh RNH, Murray-Lyon IM, Dawson JL, Pietroni MC, Williams R. Transection of the oesophagus for bleeding oesophageal varices. Brit J Surg. 1973;60:646-649.
3. Villikka K, Kivisto KT, Neuvonen PJ. The effect of rifampin on the pharmacokinetics of oral and intravenous ondansetron. Clin Pharmacol Ther. 1999;65:377-381.
4. De Witte JL, Schoenmaekers B, Sessler DI, et al. Anesth Analg. 2001;92:1319-1321.
5. Arcioni R, della Rocca M, Romanò R, et al. Anesth Analg. 2002;94:1553-1557.

Manufactured by:
Wockhardt Limited
Mumbai, India.
Distributed by:
Wockhardt USA LLC.
20 Waterview Blvd.
Parsippany, NJ 07054
USA.
Rev.260211